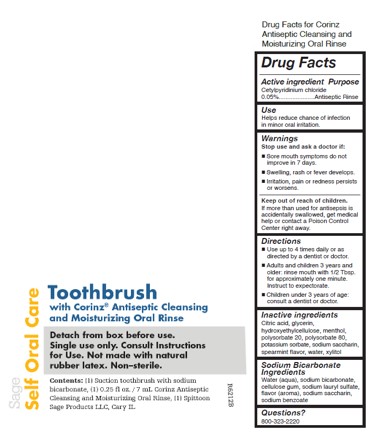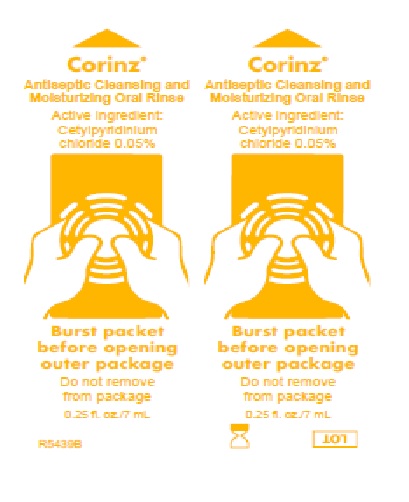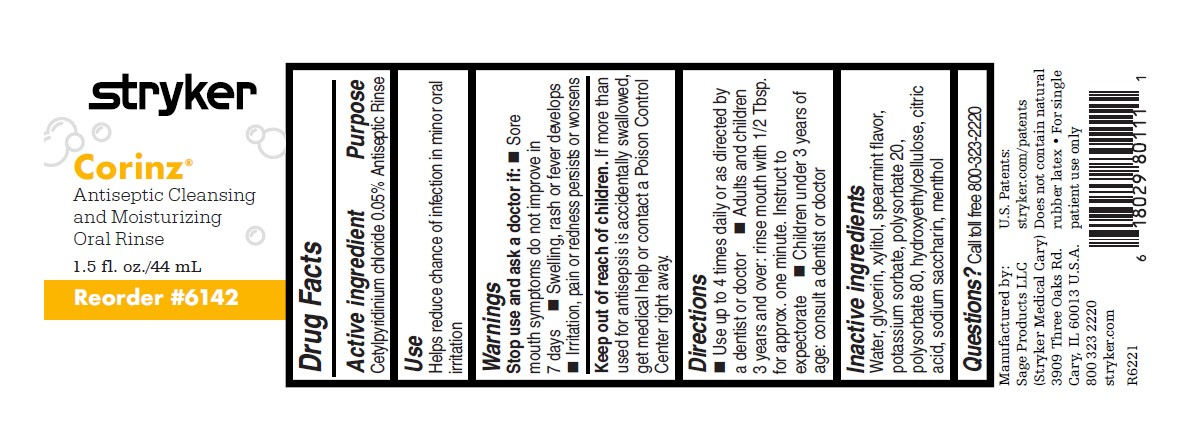 DRUG LABEL: Corinz
NDC: 53462-375 | Form: RINSE
Manufacturer: Sage Products, LLC
Category: otc | Type: HUMAN OTC DRUG LABEL
Date: 20251208

ACTIVE INGREDIENTS: CETYLPYRIDINIUM CHLORIDE 0.5 mg/1 mL
INACTIVE INGREDIENTS: WATER; GLYCERIN; XYLITOL; POTASSIUM SORBATE; POLYSORBATE 20; POLYSORBATE 80; HYDROXYETHYL CELLULOSE (4000 MPA.S AT 1%); CITRIC ACID MONOHYDRATE; SACCHARIN SODIUM; MENTHOL, UNSPECIFIED FORM

Corinz®

Drug Facts

Active ingredient: | Purpose
CORINZ ANTISEPTIC CLEANSING AND MOISTURIZING ORAL RINSE:
Cetylpyridinium chloride 0.05% | Antiseptic Rinse

Use

Helps reduce chance of infection in minor oral irritation.

Warnings

Stop use and ask a doctor if:
- Sore mouth symptoms do not improve in 7 days.
- Swelling, rash or fever develops.
- Irritation, pain or redness persists or worsens.

Keep out of reach of children.
If more than used for antisepsis is accidentally swallowed, get medical help or contact a Poison Control Center right away.

Directions

- Use up to 4 times daily or as directed by a dentist or doctor.
- Adults and children 3 years and older: rinse mouth with 1/2 Tbsp. for approx. one minute. Instruct to expectorate.
- Children under 3 years of age: consult a dentist or doctor.

Inactive ingredients

Water, glycerin, xylitol, spearmint flavor, potassium sorbate, polysorbate 20, polysorbate 80, hydroethylcellulose, citric acid, sodium saccharin, menthol

Questions?

800-323-2220.

NOT MADE WITH NATURAL RUBBER LATEX • MADE IN U.S.A.